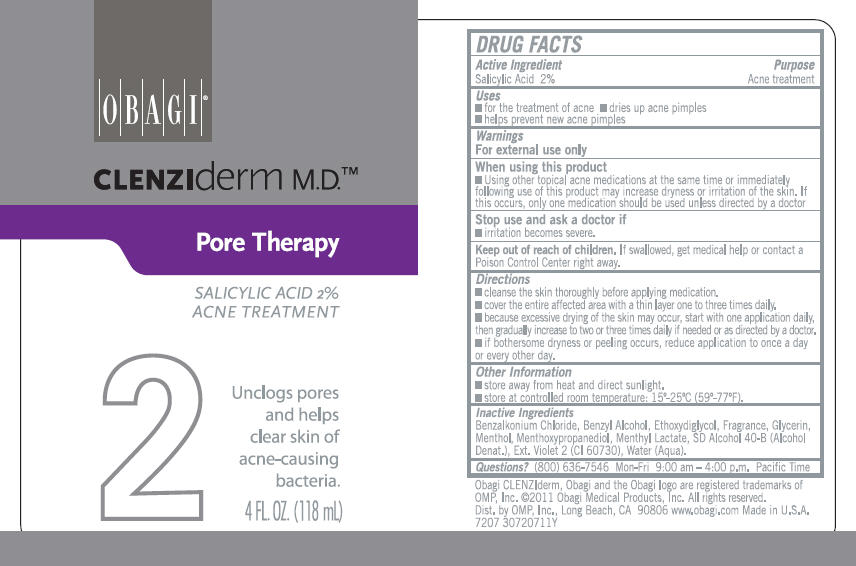 DRUG LABEL: CLENZIDERM PORE THERAPY 
NDC: 62032-110 | Form: LIQUID
Manufacturer: OMP, INC.
Category: otc | Type: HUMAN OTC DRUG LABEL
Date: 20111215

ACTIVE INGREDIENTS: SALICYLIC ACID 20 mg/1 mL
INACTIVE INGREDIENTS: ALCOHOL; DIETHYLENE GLYCOL MONOETHYL ETHER; BENZYL ALCOHOL; 3-((L-MENTHYL)OXY)PROPANE-1,2-DIOL; GLYCERIN; BENZALKONIUM CHLORIDE; MENTHOL; MENTHYL LACTATE; EXT. D&C VIOLET NO. 2; WATER

OBAGI®
CLENZIderm M.D.™
Pore Therapy

DRUG FACTS

Active Ingredient

Salicylic Acid 2%

Purpose

Acne treatment

Uses

- for the treatment of acne
- dries up acne pimples
- helps prevent new acne pimples

Warnings

For external use only

When using this product

- Using other topical acne medications at the same time or immediately following use of this product may increase dryness or irritation of the skin. If this occurs, only one medication should be used unless directed by a doctor

Stop use and ask a doctor if

- irritation becomes severe.

Keep out of reach of children. If swallowed, get medical help or contact a Poison Control Center right away.

Directions

- cleanse the skin thoroughly before applying medication.
- cover the entire affected area with a thin layer one to three times daily.
- because excessive drying of the skin may occur, start with one application daily, then gradually increase to two or three times daily if needed or as directed by a doctor.
- if bothersome dryness or peeling occurs, reduce application to once a day or every other day.

Other Information

- store away from heat and direct sunlight.
- store at controlled room temperature: 15°-25°C (59°-77°F).

Inactive Ingredients

Benzalkonium Chloride, Benzyl Alcohol, Ethoxydiglycol, Fragrance, Glycerin, Menthol, Menthoxypropanediol, Menthyl Lactate, SD Alcohol 40-B (Alcohol Denat.), Ext. Violet 2 (CI 60730), Water.

Questions?

(800) 636-7546 Mon-Fri 9:00 am – 4:00 p.m. Pacific Time

Dist. by OMP, Inc., Long Beach, CA 90806

PRINCIPAL DISPLAY PANEL - 118 mL Bottle Label

OBAGI®

CLENZIderm M.D.™

Pore Therapy

SALICYLIC ACID 2%
ACNE TREATMENT

2
Unclogs pores
and helps
clear skin of
acne-causing
bacteria.

4 FL. OZ. (118 mL)